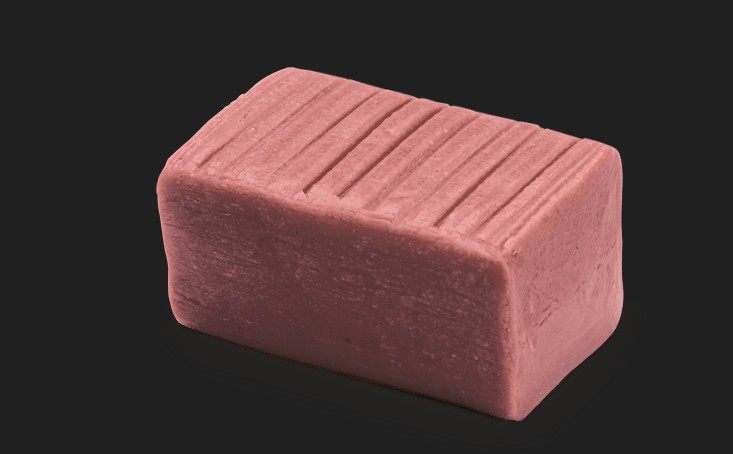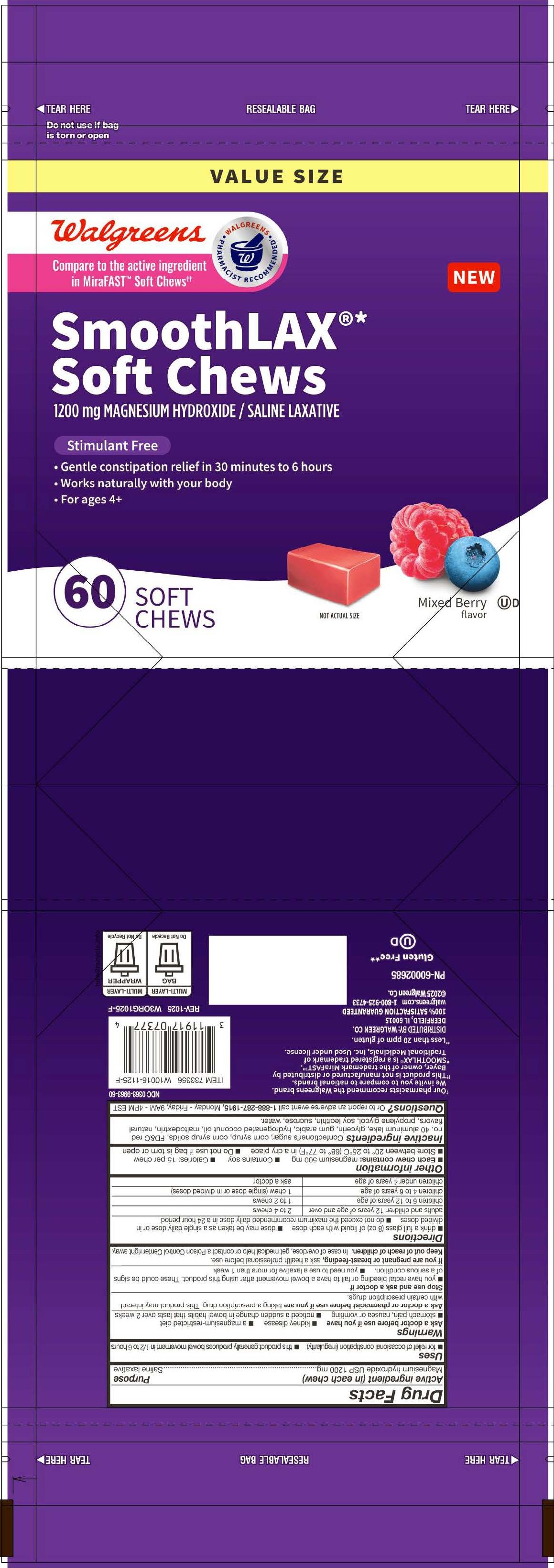 DRUG LABEL: Walgreens SmoothLAX Soft Chews
NDC: 0363-9963 | Form: TABLET, CHEWABLE
Manufacturer: Walgreens
Category: otc | Type: HUMAN OTC DRUG LABEL
Date: 20260216

ACTIVE INGREDIENTS: MAGNESIUM HYDROXIDE 1200 mg/1 1
INACTIVE INGREDIENTS: WATER

Magnesium Hydroxide 1200 mg

Active ingredient (in each chew)

Magnesium Hydroxide USP 1200 mg

Purpose

Saline laxative

Uses

- for relief of occasional constipation (irregularity)
- this product generally produces bowel movement in 1/2 to 6 hours

Warnings

Ask a doctor before use if you have

- kidney disease
- a magnesium-restricted diet
- stomach pain, nausea or vomiting
- noticed a sudden change in bowel habits that last over 2 weeks

Ask a doctor or pharmacist before use if you are taking a prescription drug. This product may interact with certainprescription drugs.

Stop use and ask doctor if

- you have rectal bleeding or fail to have a bowel movement after using this product. These could be signs of a serious condition.
- you need to use a laxative for more than 1 week

PREGNANCY OR BREAST FEEDING

If you are pregnant or breast-feeding, ask a health professional before use.

Keep out of reach of children.

OVERDOSAGE

In case of overdose, get medical help or contact Poison Control Center right away.

Directions

- drink a full glass (8oz) of liquid with each dose
- dose may be taken as a single daily dose or in divided doses
- do not exceed the maximum recommended daily dose in a 24 hour period

adults and children 12 years of age and over - 2 to 4 chews

children 6 to 12 years of age - 1 to 2 chews

children 4 to 6 years of age - 1 chew (single dose or in divided doses)

children under 4 years of age - ask a doctor

Other information

- Each chew contains: magnesium 500 mg
- Contains soy
- Calories: 15 per chew
- Store between 20° to 25°C (68° to 77°F) in a dry place
- Do not use if bag is torn or open

INACTIVE INGREDIENT

Inactive ingredients: Confectioner's sugar, corn syrup, corn syrup solids, FD&C red no. 40 aluminum lake, glycerin, gum arabic, hydrogenated coconut oil, maltodextrin, natural flavors, propylene glycol, soy lecithin, sucrose, water.

QUESTIONS

Questions? Or to report an adverse event call 1-888-287-1915, Monday - Friday, 9AM - 4PM EST